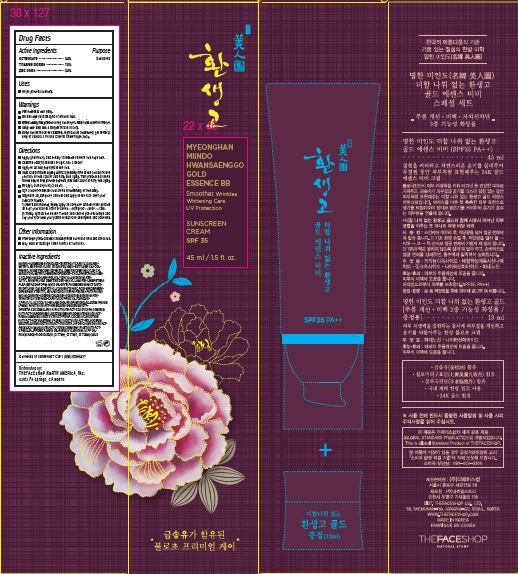 DRUG LABEL: MYEONGHAN MIINDO HWANSAENGGO GOLD ESSENCE BB SPF 35
NDC: 51523-317 | Form: CREAM
Manufacturer: THEFACESHOP CO. LTD.
Category: otc | Type: HUMAN OTC DRUG LABEL
Date: 20141120

ACTIVE INGREDIENTS: Zinc Oxide 1.35 g/45 mL; Octinoxate 2.25 g/45 mL; Titanium Dioxide 3.51 g/45 mL
INACTIVE INGREDIENTS: WATER

MYEONGHAN MIINDO HWANSAENGGO GOLD ESSENCE BB SPF 35 30100317

Active Ingredients

OCTINOXATE • • • • • • • • • • • • • • • • • • 5.0%
TITANIUM DIOXIDE • • • • • • • • • • • • • • 7.8%
ZINC OXIDE • • • • • • • • • • • • • • • • • • • .3.0%

Purpose

Sunscreen

Sunscreen

Sunscreen

Warnings

For external use only.
Do not use on damaged or broken skin.
When using this product keep out of eyes. Rinse with water to remove.
Stop use and ask a doctor if rash occurs.
If product is swallowed, get medical
help or contact a Poison Control Center right away.

Skin Cancer/Skin Aging Alert: Spending time in the sun increases
your risk of skin cancer and early skin aging. This product has been
shown only to help prevent sunburn, not skin cancer or early skin aging.

Keep out of reach of children.

Directions

Reapply at least every 2 hours.
Use a water-resistant sunscreen if swimming or sweating.
May stain or damage some fabrics or surfaces.
Dispense an adequate amount and apply to the face after your
skincare routine.
1) After basic makeup, lightly apply an adequate amount of the product
all over your face in order of cheek forehead nose chin.
2) Thinly spread out on the T zone and chin to prevent lumps and
cup your face with your palms to increase absorption and adhesion.

DOSAGE AND ADMINISTRATION

Apply generously and evenly 15 minutes before sun exposure.
Protect the product in this container from excessive heat and direct sun.
Children under 6 months of age: Ask a doctor
Apply to all skin exposed to the sun.

Other Information

Protect the product in this container from excessive heat and direct sun.
May stain or damage some fabrics or surfaces.

Inactive Ingredients

WATER•ALUMINUM HYDROXIDE•TRIETHOXYCAPRYLYLSILANE•
METHYL METHACRYLATE CROSSPOLYMER•BUTYLENE GLYCOL•
PHENYL TRIMETHICONE•DIPHENYL DIMETHICONE•HEXYLDECYL
MYRISTOYL•METHYLAMINOPROPIONATE•CYCLOPENTASILOXANE•
CYCLOHEXASILOXANE•POLYGLYCERYL-4 ISOSTEARATE•
CETYL PEG/PPG-10/1 DIMETHICONE•HEXYL LAURATE•LIMNANTHES
ALBA (MEADOWFOAM) SEED OIL•DISTEARDIMONIUM HECTORITE•
PROPYLENE CARBONATE•GLYCERIN•STEARIC ACID•NIACINAMIDE•
DIPENTAERYTHRITYL HEXAHYDROXYSTEARATE/HEXASTEARATE/
HEXAROSINATE•SODIUM CHLORIDE•SORBITAN ISOSTEARATE•
TRIHYDROXYSTEARIN•CAPRYLIC/CAPRIC GLYCERIDES•
CAPRYLYL GLYCOL•1,2-HEXANEDIOL•PROPANEDIOL•ILLICIUM VERUM
(ANISE) FRUIT EXTRACT•ADENOSINE•DISODIUM EDTA•
OPUNTIA COCCINELLIFERA FRUIT EXTRACT•CORDYCEPS SINENSIS
EXTRACT•GANODERMA LUCIDUM (MUSHROOM) STEM EXTRACT•
PANAX GINSENG ROOT EXTRACT•PORIA COCOS SCLEROTIUM
EXTRACT•ACHYRANTHES FAURIEI ROOT EXTRACT•POLYGONUM
MULTIFLORUM ROOT EXTRACT•CUSCUTA JAPONICA SEED EXTRACT•
ANGELICA GIGAS EXTRACT•LYCIUM CHINENSE FRUIT EXTRACT•
CAMELLIA JAPONICA SEED OIL•PINUS SYLVESTRIS LEAF OIL•
FRAGRANCE•IRON OXIDES (CI 77492, CI 77491, CI 77499)•GOLD

Questions or comments? Call 1 (866) 638-8417

Distributed by:

THEFACESHOP NORTH AMERICA, INC.
Santa Fe Springs, CA 90670

PACKAGE LABEL

MYEONGHAN MIINDO HWANSAENGGO GOLD ESSENCE BB